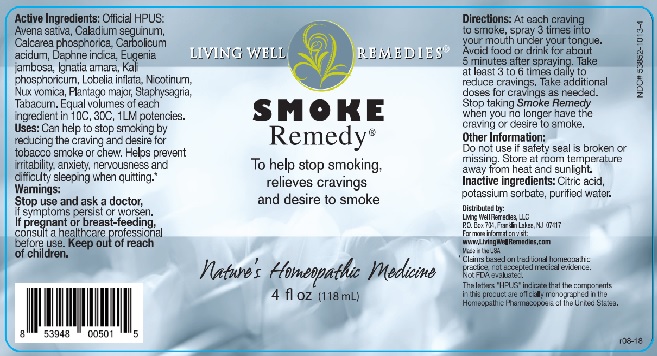 DRUG LABEL: Smoke Remedy
NDC: 53852-1013 | Form: LIQUID
Manufacturer: Living Well Remedies, LLC
Category: homeopathic | Type: HUMAN OTC DRUG LABEL
Date: 20181004

ACTIVE INGREDIENTS: AVENA SATIVA FLOWERING TOP 10 [hp_C]/118 mL; DIEFFENBACHIA SEGUINE 10 [hp_C]/118 mL; TRIBASIC CALCIUM PHOSPHATE 10 [hp_C]/118 mL; DAPHNE ODORA BARK 10 [hp_C]/118 mL; SYZYGIUM JAMBOS SEED 10 [hp_C]/118 mL; STRYCHNOS IGNATII SEED 10 [hp_C]/118 mL; DIBASIC POTASSIUM PHOSPHATE 10 [hp_C]/118 mL; STRYCHNOS NUX-VOMICA SEED 10 [hp_C]/118 mL; PLANTAGO MAJOR 10 [hp_C]/118 mL; DELPHINIUM STAPHISAGRIA SEED 10 [hp_C]/118 mL; LOBELIA INFLATA 10 [hp_C]/118 mL; NICOTINE 10 [hp_C]/118 mL; TOBACCO LEAF 10 [hp_C]/118 mL; PHENOL 10 [hp_C]/118 mL
INACTIVE INGREDIENTS: CITRIC ACID MONOHYDRATE; POTASSIUM SORBATE; water

Smoke Remedy

ACTIVE INGREDIENT

Active Ingredients: Official HPUS: Avena sativa, Caladium seguinum, Calcarea phosphorica, Carbolicum acidum, Daphne indica, Eugenia jambosa, Ignatia amara, Kali phosphoricum, Lobelia inflata, Nicotinum, Nux vomica, Plantago major, Staphysagria, Tabacum. Equal volumes of each ingredient in 10C, 30C, 1LM potencies.

The letters "HPUS" indicate that the components in this product are officially monograped in the Homeopathic Pharmacopoeia of the United States.

INDICATIONS AND USAGE

Uses: Can help to stop smoking by reducing the craving and desire for tobacco smoke or chew. Helps prevent irritability, anxiety, nervousness and difficulty sleeping when quitting.*

*Claims based on traditional homeopathic practices, not accepted medical evidence.

Not FDA Evaluated

WARNINGS

Warnings: Stop use and ask a doctor, if symptoms persist or worsen. If pregnant or breast-feeding, consult a health care professional before use.

Keep out of reach of children.

DOSAGE AND ADMINISTRATION

Directions: At each craving to smoke, spray 3 times into your mouth under your tongue. Avoid food or drink for about 5 after spraying. Take at least 3 to 6 times daily to reduce cravings. Take additional doses for cravings as needed. Stop taking Smoke Remedy when you no longer have the craving or desire to smoke.

Other Information: Do not use if safety seal is broken or missing. Store at room temperature away from heat and sunlight.

INACTIVE INGREDIENT

Inactive ingredients: Bio-Energetically enhanced pure water, citric acid, potassium sorbate.

QUESTIONS

Distributed by:

Living Well Remedies, LLC

P.O. Box 704, Franklin Lakes, NJ 07417

For more information visit

www.LivingWellRemedies.com

Made in the USA

PACKAGE LABEL

LIVING WELL REMEDIES

SMOKE

Remedy®

To help stop smoking,

relieves cravings

and desire to smoke

Nature's Homeopathic Medicine

PURPOSE

To help stop smoking,

relieves cravings

and desire to smoke